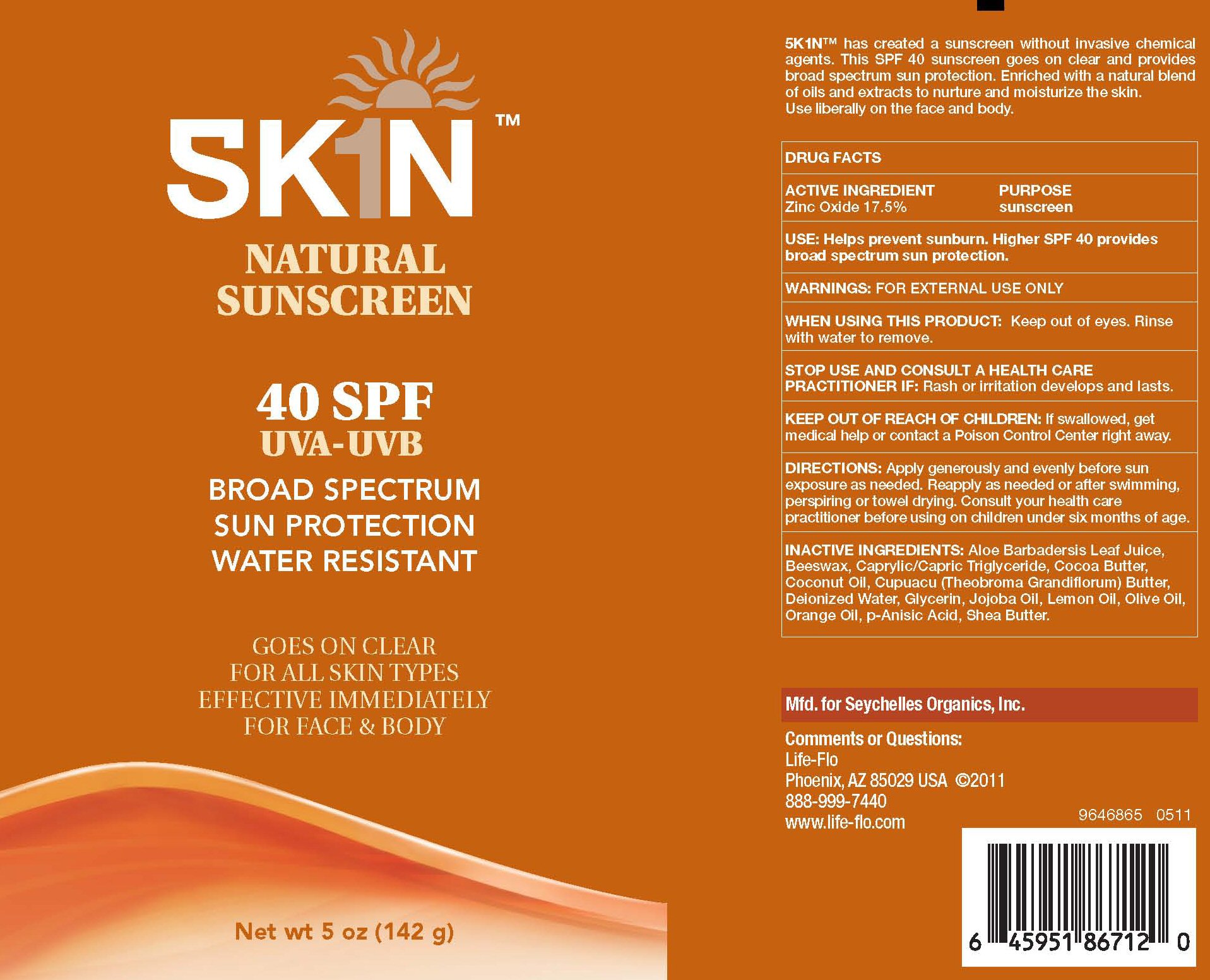 DRUG LABEL: SK1N NATURAL SUNSCREEN SPF 40
NDC: 76245-102 | Form: LOTION
Manufacturer: True Nature Group, Inc.
Category: otc | Type: HUMAN OTC DRUG LABEL
Date: 20110615

ACTIVE INGREDIENTS: ZINC OXIDE 25 g/142 g
INACTIVE INGREDIENTS: ALOE VERA LEAF; YELLOW WAX; MEDIUM-CHAIN TRIGLYCERIDES; COCOA BUTTER; COCONUT OIL; THEOBROMA GRANDIFLORUM SEED BUTTER; WATER; GLYCERIN; JOJOBA OIL; LEMON OIL; OLIVE OIL; ORANGE OIL; P-ANISIC ACID; SHEA BUTTER

WARNINGS

WARNING: FOR EXTERNAL USE ONLY
WHEN USING THIS PRODUCT: KEEP OUT OF THE EYES. RINSE WITH WATER TO REMOVE.
STOP USE AND CONSULT A HEALTH CARE PRACTITIONER IF:RASH OR IRRITATION DEVELOPS AND LASTS.
KEEP OUT OF REACH OF CHILDREN: IF SWALLOWED, GET MEDICAL HELP OR CONTACT A POISON CONTROL CENTER RIGHT AWAY.

SK1N NATURAL SUNSCREEN 40 SPF LABEL

SKIN NATURAL SUNSCREEN TM DAILY MOISTURIZER 40 SPF UVA-UVB SUN PROTECTION BROAD SPECTRUM SUN PROTECTION WATER RESISTANT
GOES ON CLEAR FOR ALL SKIN TYPES EFFECTIVE IMMEDIATELY FOR FACE AND BODY NET WT 5 OZ (142G)
SK1N TM HAS CREATED A SUNSCREEN WITHOUT INVASIVE CHEMICAL AGENTS. THIS SPF 40 SUNSCREEN GOES ON CLEAR AND PROVIDES BROAD SPECTRUM SUN PROTECTION.. ENRICHED WITH A NATURAL BLEND OF OILS AND EXTRACTS TO NURTURE AND MOISTURIZE THE SKIN. USE LIBERALLY ON THE FACE AND BODY.
DRUG FACTS ACTIVE INGREDIENT ZINC OXIDE 17.5% PURPOSE SUNSCREEN
USE: HELPS PREVENT SUNBURN. HIGHER SPF 40 PROVIDES BROAD SPECTRUM SUN PROTECTION..
DIRECTIONS: APPLY GENEROUSLY AND EVENLY BEFORE SUN EXPOSURE AS NEEDED. REAPPLY AS NEEDED OR AFTER SWIMMING, PERSPIRING OR TOWEL DRYING. CONSULT YOUR HEALTH CARE PRACTITIONER BEFORE USING ON CHILDREN UNDER SIX MONTHS OF AGE.
INACTIVE INGREDIENTS: ALOE BARBADENSIS LEAF JUICE, BEESWAX, CAPRYLIC/CAPRIC TRIGLYCERIDE, COCOA BUTTER, COCONUT OIL, CUPUACU (THEOBROMA GRANDIFLORUM) BUTTER, DEONIZED WATER, GLYCERIN, JOJOBA OIL, LEMON OIL, OLIVE OIL, ORANGE OIL, P-ANISIC ACID, SHEA BUTTER.
MFD. FOR SEYCHELLES ORGANICS, INC. COMMENTS OR QUESTIONS: LIFE-FLO PHOENIX, AZ 85029 USA C2011 888-999-7440 WWW.LIFE-FLO.COM 9646865 0511 6 4595186712 0